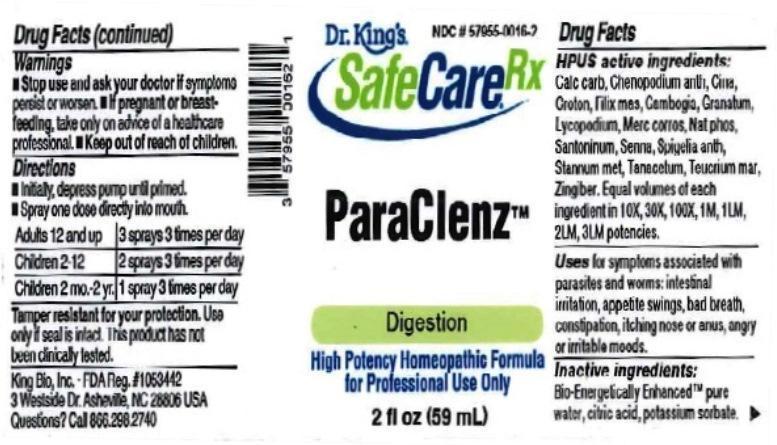 DRUG LABEL: ParaClenz
NDC: 57955-0016 | Form: LIQUID
Manufacturer: King Bio Inc.
Category: homeopathic | Type: HUMAN OTC DRUG LABEL
Date: 20161103

ACTIVE INGREDIENTS: OYSTER SHELL CALCIUM CARBONATE, CRUDE 10 [hp_X]/59 mL; DYSPHANIA AMBROSIOIDES 10 [hp_X]/59 mL; ARTEMISIA CINA PRE-FLOWERING TOP 10 [hp_X]/59 mL; CROTON TIGLIUM SEED 10 [hp_X]/59 mL; DRYOPTERIS FILIX-MAS ROOT 10 [hp_X]/59 mL; GAMBOGE 10 [hp_X]/59 mL; PUNICA GRANATUM ROOT BARK 10 [hp_X]/59 mL; LYCOPODIUM CLAVATUM SPORE 10 [hp_X]/59 mL; MERCURIC CHLORIDE 10 [hp_X]/59 mL; SODIUM PHOSPHATE, DIBASIC, HEPTAHYDRATE 10 [hp_X]/59 mL; SANTONIN 10 [hp_X]/59 mL; SENNA LEAF 10 [hp_X]/59 mL; SPIGELIA ANTHELMIA 10 [hp_X]/59 mL; TIN 10 [hp_X]/59 mL; TANACETUM VULGARE TOP 10 [hp_X]/59 mL; TEUCRIUM MARUM 10 [hp_X]/59 mL; GINGER 10 [hp_X]/59 mL
INACTIVE INGREDIENTS: WATER; ANHYDROUS CITRIC ACID; POTASSIUM SORBATE

ParaClenz™

ACTIVE INGREDIENT

Drug Facts__________________________________________________________________________________________________________

HPUS active ingredients: Calcarea carbonica, Chenopodium anthelminticum, Cina, Croton tiglium, Filix mas, Gambogia, Granatum, Lycopodium clavatum, Mercurius corrosivus, Natrum phosphoricum, Santoninum, Senna, Spigelia anthelmia, Stannum metallicum, Tanacetum vulgare, Teucrium marum, Zingiber officinale. Equal volumes of each ingredient in 10X, 30X, 100X, 1M, 1LM, 2LM, 3LM potencies.

INDICATIONS AND USAGE

Uses for symptoms associated with parasites and worms: intestinal irritation, appetite swings, bad breath, constipation, itching nose or anus, angry or irritable moods.

Inactive Ingredients:

Bio-Energetically Enhanced™ pure water, citric acid and potassium sorbate.

Warnings

- Stop use and ask your doctor if symptoms persist or worsen.
- If pregnant or breast-feeding, take only on advice of a healthcare professional.

- Keep out of reach of children.

Directions

- Initially, depress pump until primed.
- Spray one dose directly into mouth.
- Adults 12 and up: 3 sprays 3 times per day
- Children 2-12: 2 sprays 3 times per day
- Children 2 mo.-2 yr.: 1 spray 3 times per day

OTHER SAFETY INFORMATION

Tamper resistant for your protection. Use only if safety seal is intact. This product has not been independently tested.

PURPOSE

Uses for symptoms associated with parasites and worms:

- intestinal irritation
- appetite swings
- bad breath
- constipation
- itching nose or anus
- angry or irritable moods